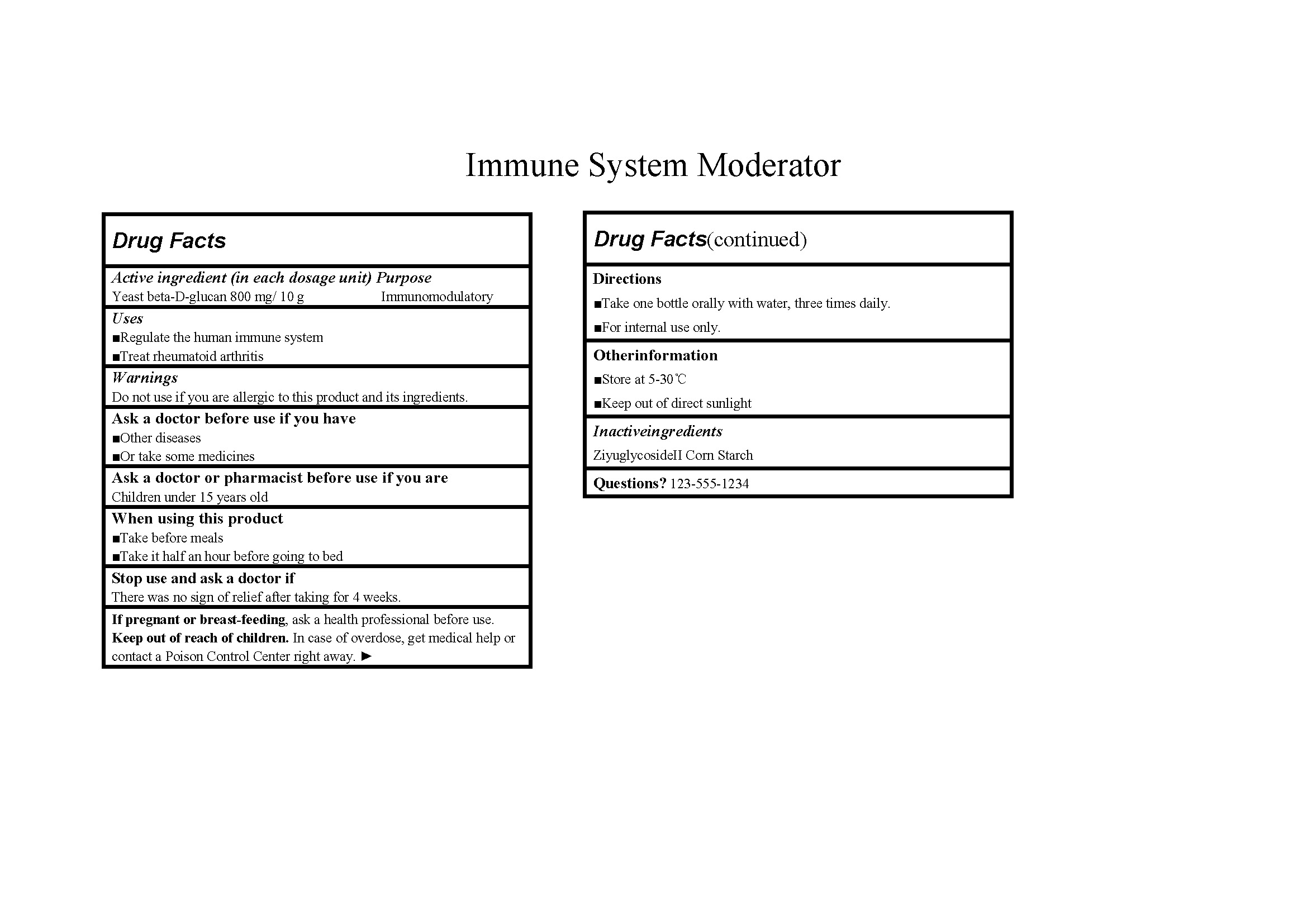 DRUG LABEL: Immune System Moderator
NDC: 84611-101 | Form: GRANULE
Manufacturer: Sanaura Group LIMITED
Category: otc | Type: HUMAN OTC DRUG LABEL
Date: 20240815

ACTIVE INGREDIENTS: YEAST .BETA.-D-GLUCAN 800 mg/10 g
INACTIVE INGREDIENTS: STARCH, CORN; ZIYUGLYCOSIDE II

Immune System Moderator 84611-101

Active ingredient: YEAST .BETA.-D-GLUCAN 800 mg/ 10 g

Purpose: Immunomodulatory

INDICATIONS AND USAGE

Use to:

Regulate the human immune system; Treat rheumatoid arthritis

WARNINGS

Warnings: Do not use if you are allergic to this product and its ingredients.

Ask a doctor or pharmacist before use if you are:

Children under 15 years old

Ask a doctor before use if you have

Other diseases, Or take some medicines

When using this product:

Take before meals, Take it half an hour before going to bed

Stop use and ask a doctor if:

There was no sign of relief after taking for 4 weeks.

PREGNANCY OR BREAST FEEDING

If pregnant or breast-feeding, ask a health professional before use.

Keep out of reach of children. In case of overdose, get medical help or contact a Poison Control Center right away.

Directions:

Take one bottle orally with water, three times daily.

For internal use only.

Other information:

Store at 5-30℃;

Keep out of direct sunlight

Inactive ingredients: ZIYUGLYCOSIDE II, Corn Starch

Questions? 123-555-1234

Label